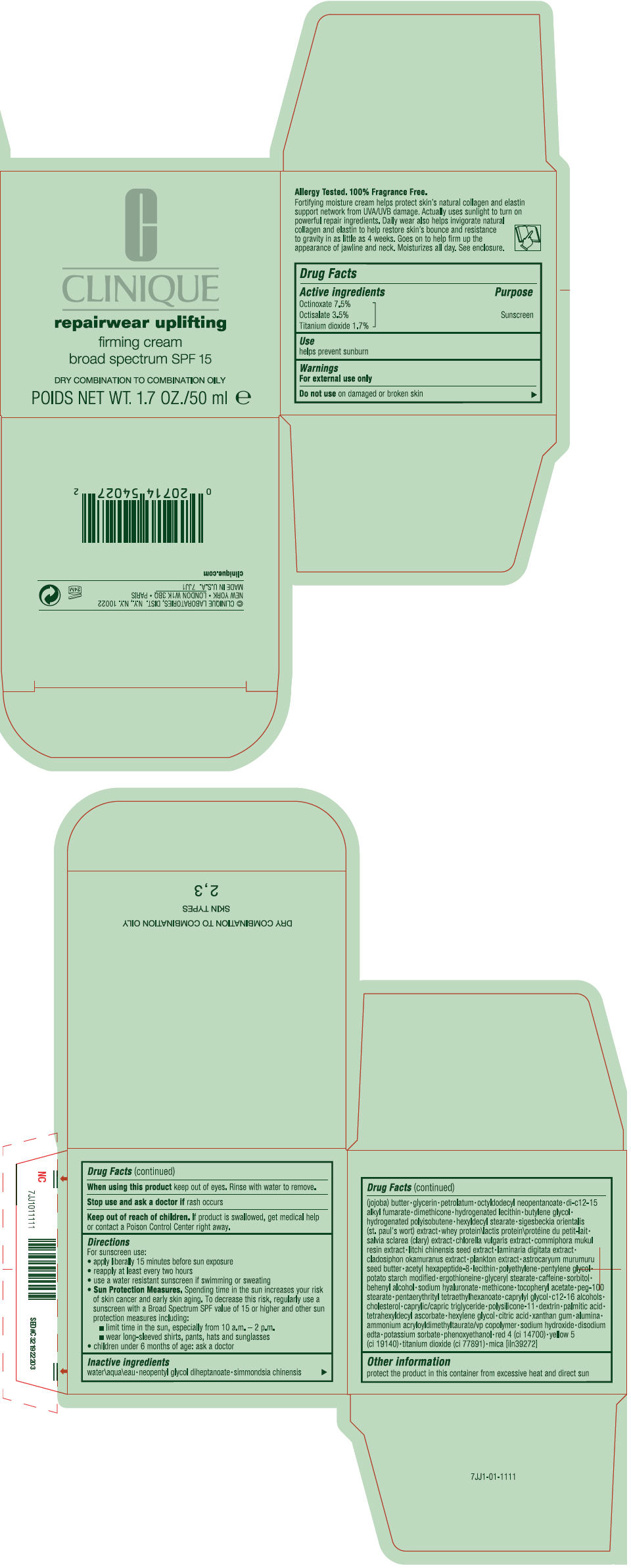 DRUG LABEL: CLINIQUE 
NDC: 49527-014 | Form: CREAM
Manufacturer: CLINIQUE LABORATORIES INC
Category: otc | Type: HUMAN OTC DRUG LABEL
Date: 20120816

ACTIVE INGREDIENTS: OCTINOXATE 7.5 mL/100 mL; OCTISALATE 3.5 mL/100 mL; TITANIUM DIOXIDE 1.7 mL/100 mL
INACTIVE INGREDIENTS: water; neopentyl glycol diheptanoate; glycerin; petrolatum; octyldodecyl neopentanoate; di-c12-15 alkyl fumarate; dimethicone; butylene glycol; hexyldecyl stearate; chlorella vulgaris; guggul; litchi chinensis seed; laminaria digitata; cladosiphon okamuranus; astrocaryum murumuru seed butter; acetyl hexapeptide-8; high density polyethylene; pentylene glycol; ergothioneine; glyceryl monostearate; caffeine; sorbitol; docosanol; hyaluronate sodium; .alpha.-tocopherol acetate; peg-100 stearate; pentaerythrityl tetraethylhexanoate; caprylyl glycol; c12-16 alcohols; cholesterol; medium-chain triglycerides; icodextrin; palmitic acid; tetrahexyldecyl ascorbate; hexylene glycol; citric acid monohydrate; xanthan gum; aluminum oxide; ammonium acryloyldimethyltaurate/vp copolymer; sodium hydroxide; edetate disodium; potassium sorbate; phenoxyethanol; FD&C red no. 4; FD&C yellow no. 5; mica

REPAIRWEAR UPLIFTING FIRMING CREAM BROAD SPECTRUM SPF 15 DRY COMBO OILY

Drug Facts

Active ingredients

Octinoxate 7.5%
Octisalate 3.5%
Titanium dioxide 1.7%

Purpose

Sunscreen

Use

helps prevent sunburn

Warnings

For external use only

Do not use on damaged or broken skin

When using this product keep out of eyes. Rinse with water to remove.

Stop use and ask a doctor if rash occurs

Keep out of reach of children. If product is swallowed, get medical help or contact a Poison Control Center right away.

Directions

For sunscreen use:

- apply liberally 15 minutes before sun exposure
- reapply at least every two hours
- use a water resistant sunscreen if swimming or sweating
- Sun Protection Measures. Spending time in the sun increases your risk of skin cancer and early skin aging. To decrease this risk, regularly use a sunscreen with a Broad Spectrum SPF value of 15 or higher and other sun protection measures including:
  - limit time in the sun, especially from 10 a.m. – 2 p.m.
  - wear long-sleeved shirts, pants, hats and sunglasses
- children under 6 months of age: ask a doctor

Inactive ingredients

water\aqua\eau • neopentyl glycol diheptanoate • simmondsia chinensis (jojoba) butter • glycerin • petrolatum • octyldodecyl neopentanoate • di-c12-15 alkyl fumarate • dimethicone • hydrogenated lecithin • butylene glycol • hydrogenated polyisobutene • hexyldecyl stearate • sigesbeckia orientalis (st. paul's wort) extract • whey protein\lactis protein\protéine du petit-lait • salvia sclarea (clary) extract • chlorella vulgaris extract • commiphora mukul resin extract • litchi chinensis seed extract • laminaria digitata extract • cladosiphon okamuranus extract • plankton extract • astrocaryum murumuru seed butter • acetyl hexapeptide-8 • lecithin • polyethylene • pentylene glycol • potato starch modified • ergothioneine • glyceryl stearate • caffeine • sorbitol • behenyl alcohol • sodium hyaluronate • methicone • tocopheryl acetate • peg-100 stearate • pentaerythrityl tetraethylhexanoate • caprylyl glycol • c12-16 alcohols • cholesterol • caprylic/capric triglyceride • polysilicone-11 • dextrin • palmitic acid • tetrahexyldecyl ascorbate • hexylene glycol • citric acid • xanthan gum • alumina • ammonium acryloyldimethyltaurate/vp copolymer • sodium hydroxide • disodium edta • potassium sorbate • phenoxyethanol • red 4 (ci 14700) • yellow 5 (ci 19140) • titanium dioxide (ci 77891) • mica [iln39272]

Other information

protect the product in this container from excessive heat and direct sun

PRINCIPAL DISPLAY PANEL - 50 ml Jar Carton

CLINIQUE

repairwear uplifting

firming cream
broad spectrum SPF 15

DRY COMBINATION TO COMBINATION OILY

POIDS NET WT. 1.7 OZ./50 ml e